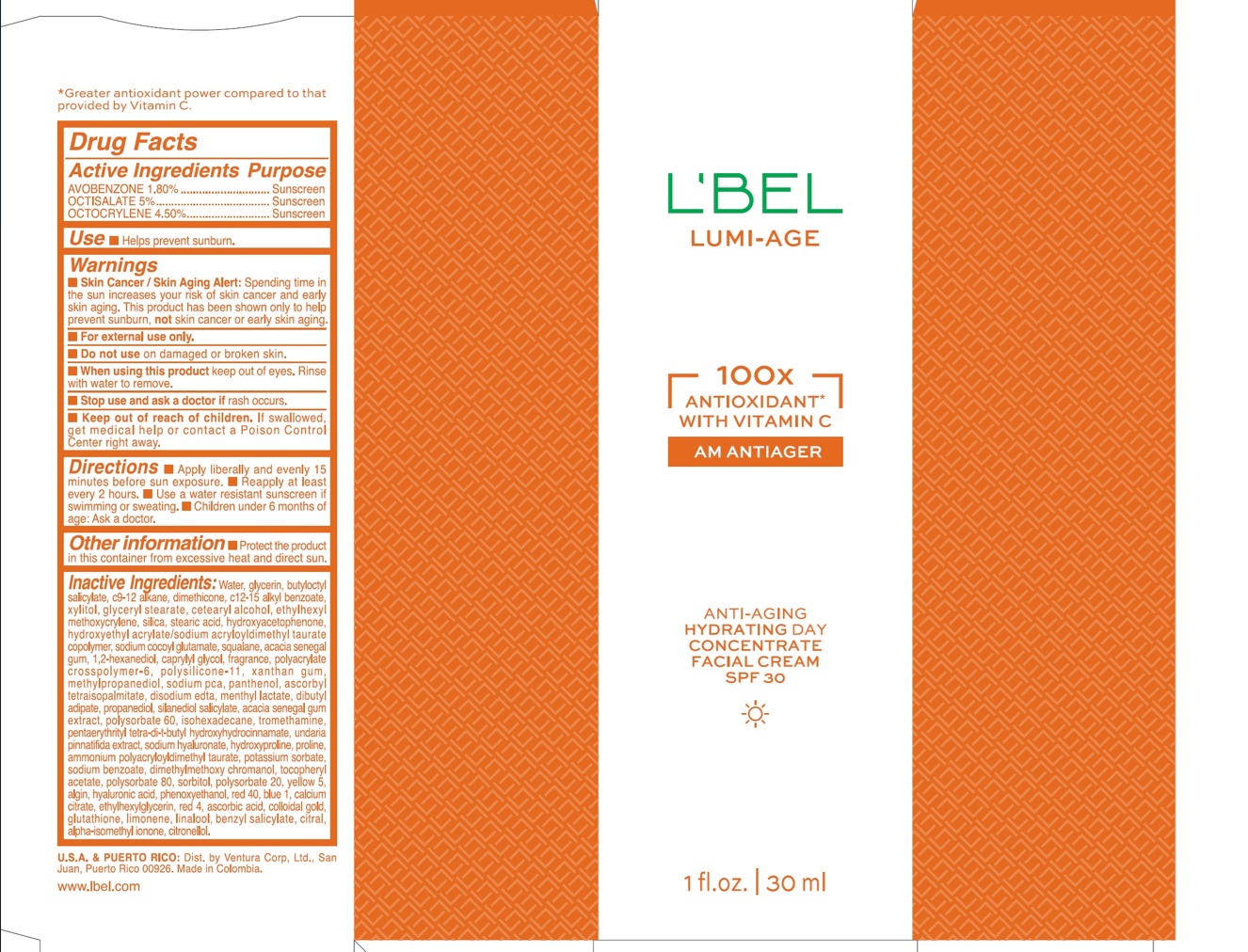 DRUG LABEL: LBEL LUMI-AGE ANTI-AGING HYDRATING DAY FACIAL SPF 30
NDC: 14141-376 | Form: EMULSION
Manufacturer: BEL STAR S.A.
Category: otc | Type: HUMAN OTC DRUG LABEL
Date: 20250303

ACTIVE INGREDIENTS: OCTISALATE 50 mg/1 mL; OCTOCRYLENE 45 mg/1 mL; AVOBENZONE 18 mg/1 mL
INACTIVE INGREDIENTS: WATER; SODIUM COCOYL GLUTAMATE; 1,2-HEXANEDIOL; CALCIUM CITRATE; RED 4; LIMONENE, (+/-)-; SILICON DIOXIDE; EDETATE DISODIUM; POTASSIUM SORBATE; LINALOOL, (+/-)-; ALPHA-TOCOPHEROL ACETATE; POLYSORBATE 80; GLUTATHIONE; GLYCERYL STEARATE; ETHYLHEXYL METHOXYCRYLENE; ISOHEXADECANE; CETEARYL ALCOHOL; HYDROXYETHYL ACRYLATE/SODIUM ACRYLOYLDIMETHYL TAURATE COPOLYMER (45000 MPA.S AT 1%); ACACIA SENEGAL GUM; SQUALANE; GLYCERIN; SODIUM PCA; SILANEDIOL SALICYLATE; HYDROXYPROLINE; STEARIC ACID; MENTHYL LACTATE; SODIUM HYALURONATE; PROLINE; ALPHA-ISOMETHYL IONONE; DIMETHICONE; C12-15 ALKYL BENZOATE; XYLITOL; PANTHENOL; DIBUTYL ADIPATE; POLYSORBATE 60; UNDARIA PINNATIFIDA; SORBITOL; POLYSORBATE 20; COLLOIDAL GOLD; CAPRYLYL GLYCOL; POLYACRYLATE CROSSPOLYMER-6; XANTHAN GUM; METHYLPROPANEDIOL; ASCORBYL TETRAISOPALMITATE; AMMONIUM POLYACRYLOYLDIMETHYL TAURATE; DIMETHYLMETHOXY CHROMANOL; YELLOW 5; PROPANEDIOL; SODIUM BENZOATE; CITRONELLOL; BENZYL SALICYLATE; ALGIN; BLUE 1; ETHYLHEXYLGLYCERIN; CITRAL; BUTYLOCTYL SALICYLATE; HYDROXYACETOPHENONE; PHENOXYETHANOL; RED 40; HYALURONIC ACID; C9-12 ALKANE; TROMETHAMINE; PENTAERYTHRITYL TETRA-DI-T-BUTYL HYDROXYHYDROCINNAMATE; ASCORBIC ACID

LBEL LUMI-AGE ANTI-AGING HYDRATING DAY CONCENTRATE FACIAL CREAM SPF 30

Active Ingredients

AVOBENZONE 1.80 %
OCTISALATE 5 %
OCTOCRYLENE 4.50 %

Purpose

Sunscreen

Uses

- Helps prevent sunburn

Warnings

- Skin Cancer / Skin Aging Alert: Spending time in the sun increases your risk of skin cancer and early skin aging. This product has been shown only to help prevent sunburn, not skin cancer or early skin aging.
- For external use only.

Do not use

on damaged or broken skin.

When using this product

keep out of eyes. Rinse with water to remove.

Stop use and ask a doctor if

rash occurs.

Keep out of reach of children.

If swallowed, get medical help or contact a Poison Control Center right away.

Directions

- Apply liberally and evenly 15 minutes before sun exposure.
- Reapply at least every 2 hours
- Use a water resistant sunscreen if swimming or sweating.
- Children under 6 months of age: Ask a doctor

Other information

- Protect the product in this container from excessive heat and direct sun.

Inactive ingredients

Water, glycerin, butyloctyl salicylate, c9-12 alkane, dimethicone, c12-15 alkyl benzoate, xylitol, glyceryl stearate, cetearyl alcohol, ethylhexyl methoxycrylene, silica, stearic acid, hydroxyacetophenone, hydroxyethyl acrylate/sodium acryloyldimethyl taurate copolymer, sodium cocoyl glutamate, squalane, acacia senegal gum, 1,2-hexanediol, caprylyl glycol, fragrance, polyacrylate crosspolymer-6, polysilicone-11, xanthan gum, methylpropanediol, sodium pca, panthenol, ascorbyl tetraisopalmitate, disodium edta, menthyl lactate, dibutyl adipate, propanediol, silanediol salicylate, acacia senegal gum extract, polysorbate 60, isohexadecane, tromethamine, pentaerythrityl tetra-di-t-butyl hydroxyhydrocinnamate, undaria pinnatifida extract, sodium hyaluronate, hydroxyproline, proline, ammonium polyacryloyldimethyl taurate, potassium sorbate, sodium benzoate, dimethylmethoxy chromanol, tocopheryl acetate, polysorbate 80, sorbitol, polysorbate 20, yellow 5, algin, hyaluronic acid, phenoxyethanol, red 40, blue 1, calcium citrate, ethylhexylglycerin, red 4, ascorbic acid, colloidal gold, glutathione, limonene, linalool, benzyl salicylate, citral, alpha-isomethyl ionone, citronellol.